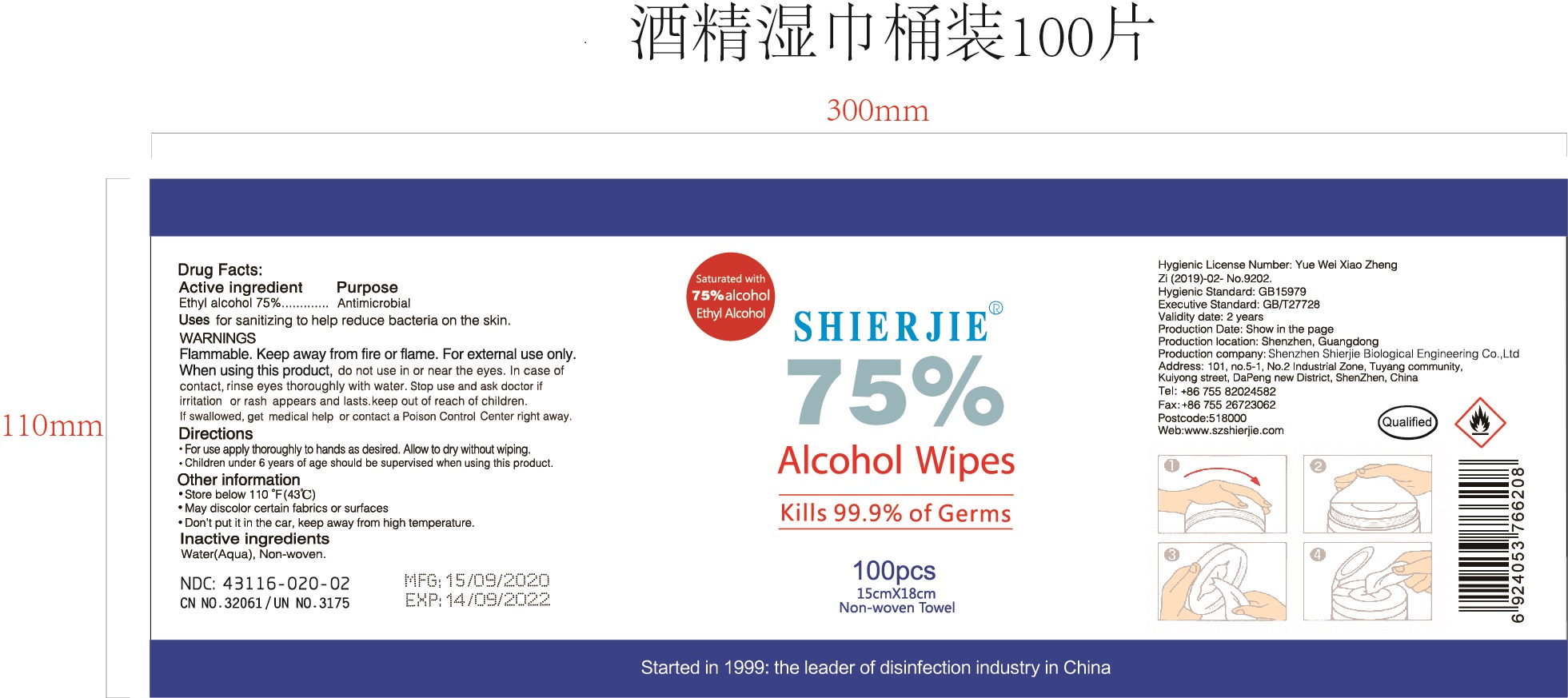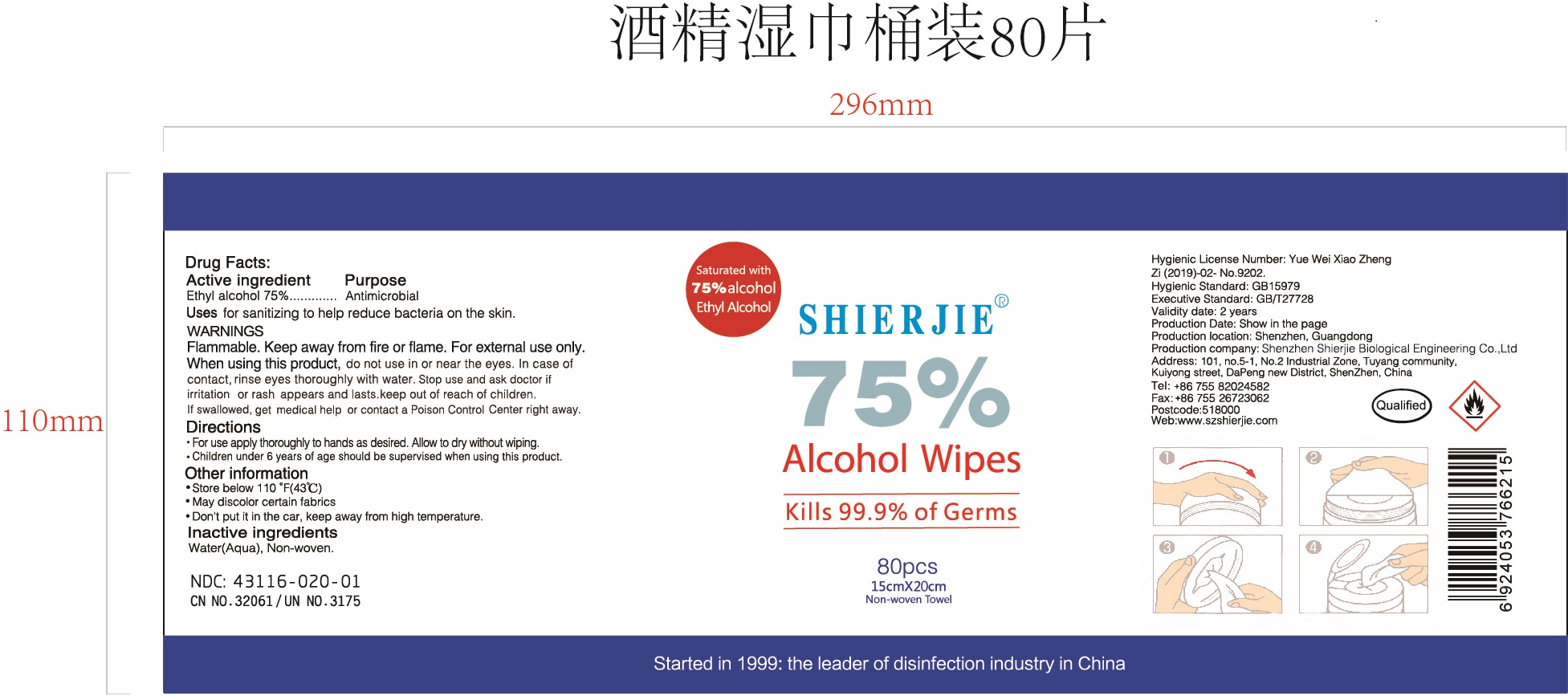 DRUG LABEL: SHIERJIE 75% Alcohol Wipes
NDC: 43116-020 | Form: CLOTH
Manufacturer: Shenzhen Shierjie Biological Engineering Co., LTD
Category: otc | Type: HUMAN OTC DRUG LABEL
Date: 20201122

ACTIVE INGREDIENTS: ALCOHOL 75 mL/100 1
INACTIVE INGREDIENTS: WATER

43116-020
SHIERJIE 75% Alcohol Wipes

Active Ingredient

Ethyl Alcohol 75%

Purpose

Antimicrobial

Uses

It is mainly used for cleaning and disinfecting skin and appliances.

Warnings

Flammable. Keep away from fire or flame. For external use only.

do not use in or near the eyes. In case of contact, rinse eyes thoroughly with water.

When using this product, do not use in or near the eyes. In case of contact, rinse eyes thoroughly with water. Stop use and ask doctor if irritation or rash appears and lasts.keep out of reach of children.
If swallowed, get medical help or contact a Poison Control Center right away.

Stop use and ask doctor if irritation or rash appears and lasts.

keep out of reach of children.
If swallowed, get medical help or contact a Poison Control Center right away.

Directions

• For use apply thoroughly to hands as desired. Allow to dry without wiping.
• Children under 6 years of age should be supervised when using this product.

Other information

• Store below 110° F(43°C)
• May discolor certain fabrics or surfaces
• Don't put it in the car, keep away from high temperature.

Inactive ingredients

Water(Aqua),Non-woven